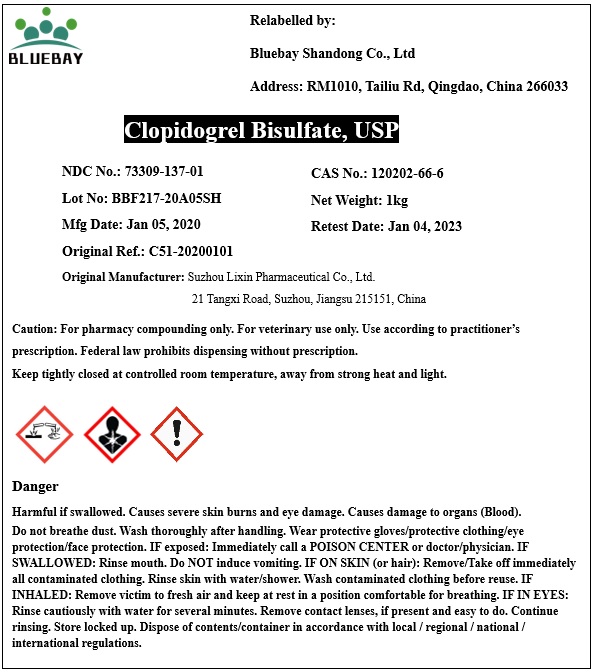 DRUG LABEL: Clopidogrel Bisulfate
NDC: 73309-137 | Form: POWDER
Manufacturer: BLUEBAY SHANDONG CO.,LTD
Category: other | Type: BULK INGREDIENT
Date: 20200525

ACTIVE INGREDIENTS: CLOPIDOGREL BISULFATE 1 kg/1 kg

Clopidogrel Bisulfate